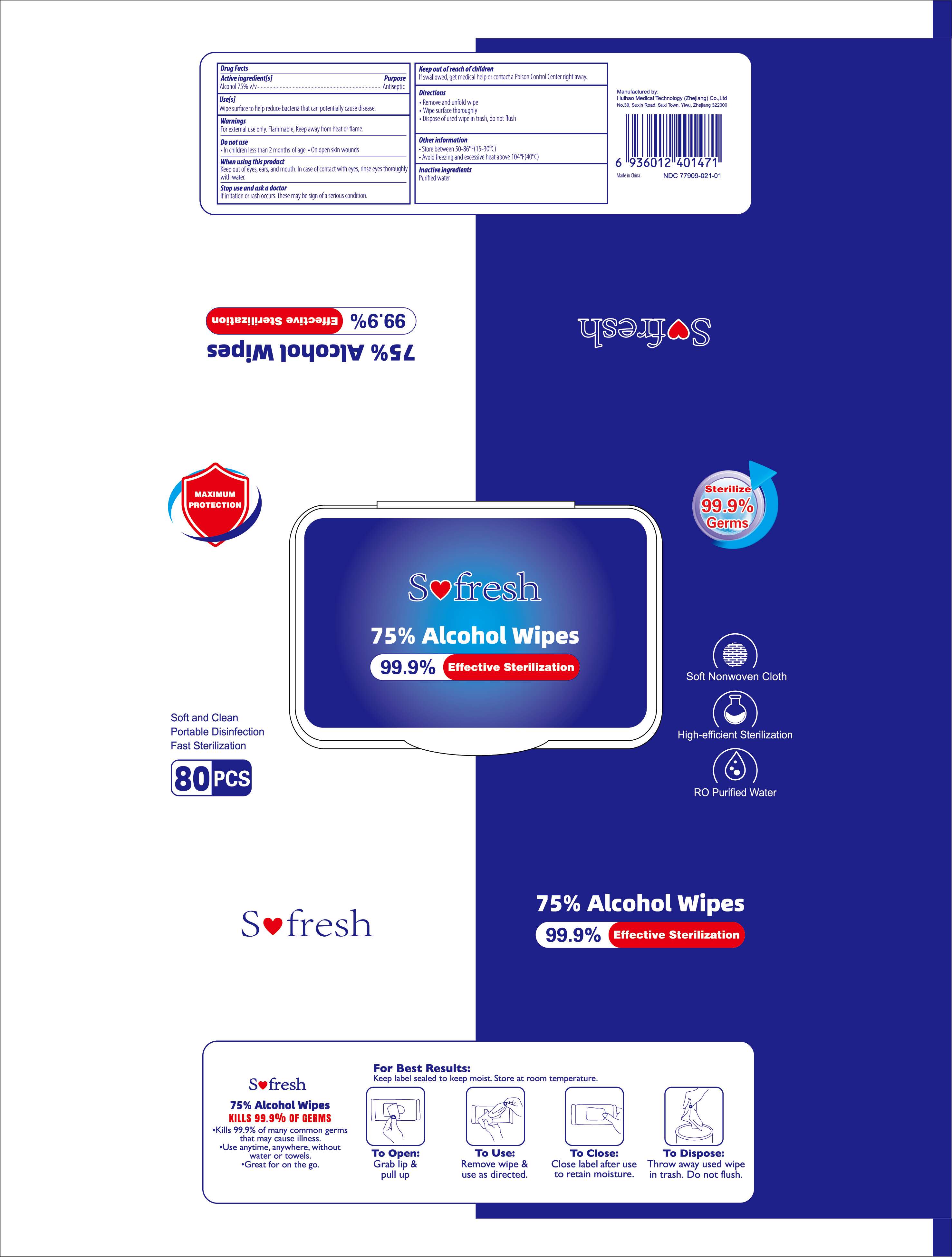 DRUG LABEL: Alcohol Wipes
NDC: 77909-021 | Form: CLOTH
Manufacturer: Huihao Medical Technology (Zhejiang) Co., Ltd
Category: otc | Type: HUMAN OTC DRUG LABEL
Date: 20201210

ACTIVE INGREDIENTS: ALCOHOL 75 mL/100 1
INACTIVE INGREDIENTS: WATER

77909-021
Alcohol Wipes

Active Ingredient(s)

Alcohol 75% v/v

Use

Wipe surface to hel[P redu1Je bacteria that can potientially cause disease.

Do not use

In chilldren less than 2 months of age. On open skin wounds

WHEN USING

Keep out of eyes, ears, and mouth. In case of contact witih eyes, rinse eyes thoroughly with water.

STOP USE

if irritation or rash occurs. These may be sign of a serious condition.

KEEP OUT OF REACH OF CHILDREN

if swallowed, get medical help or contact a Poison control Genter right way.

Directions

Rermove and unfold wipe
Wipe surface thoroughly
Dispose of used wipe in trash, do not flush

Other information

Store between 50-86°F(15-30°C)
Avoid Freezing and excessive heat above 104°F(40°c)

Inactive ingredients

Purified water